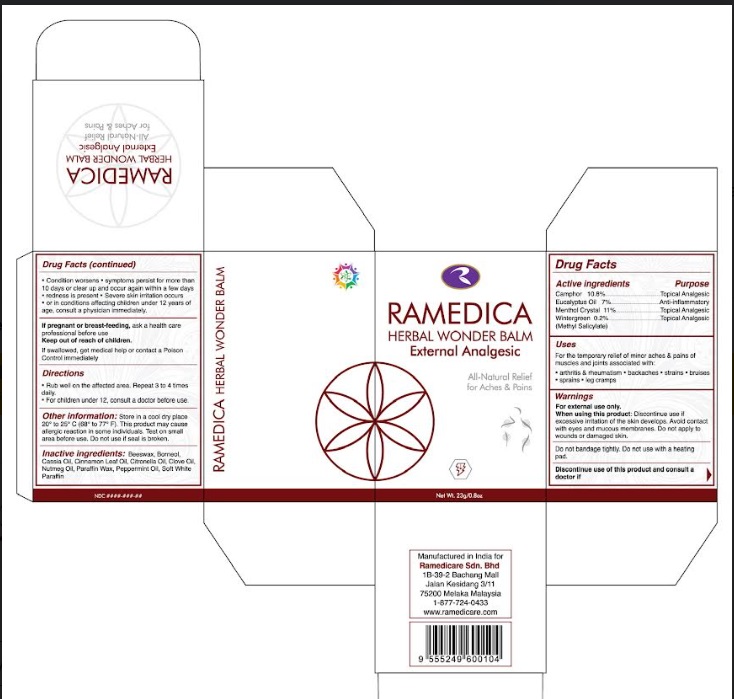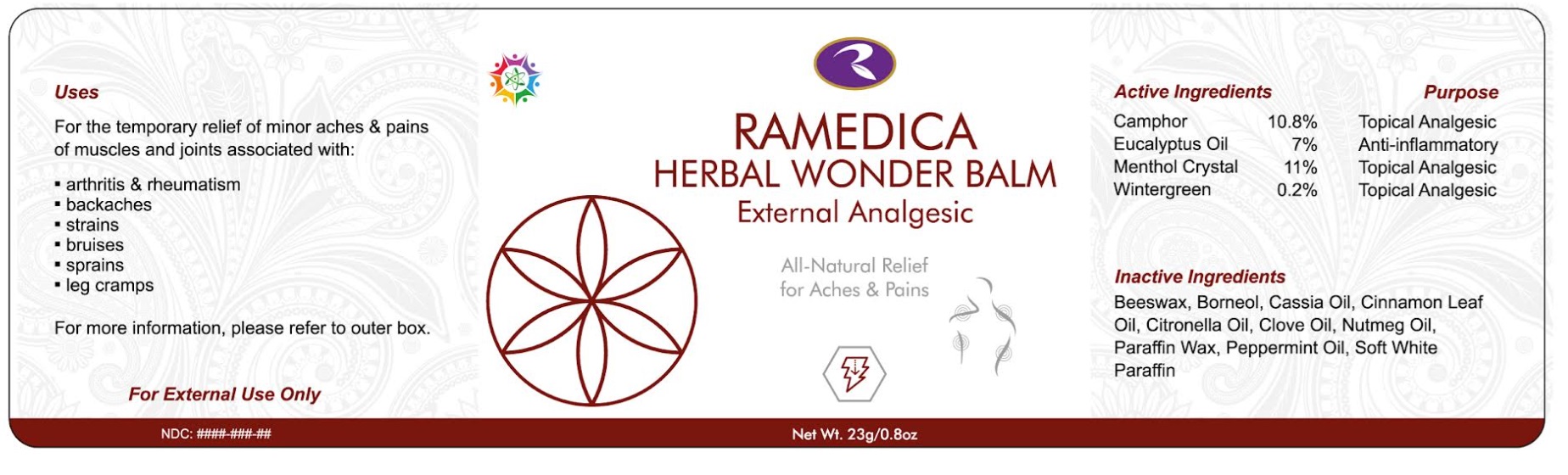 DRUG LABEL: Ramedica Herbal Wonder Balm
NDC: 66059-0004 | Form: OINTMENT
Manufacturer: Ramedicare Sdn. Bhd.
Category: otc | Type: HUMAN OTC DRUG LABEL
Date: 20241118

ACTIVE INGREDIENTS: CAMPHOR (NATURAL) 10.8 g/100 g; METHYL SALICYLATE 0.2 g/100 g; EUCALYPTUS OIL 7 g/100 g; MENTHOL 11 g/100 g
INACTIVE INGREDIENTS: BORNEOL; CHINESE CINNAMON OIL; YELLOW WAX; CINNAMON LEAF OIL; CITRONELLA OIL; CLOVE OIL; NUTMEG OIL; PARAFFIN; WHITE PETROLATUM; PEPPERMINT OIL

Active Ingredients

Camphor 10.8%

Wintergreen Oil (Methyl Salicylate) 0.2%

Eucalyptus Oil 7%

Menthol 11%

Purpose

Camphor 10.8%................................Topical Analgesic
Eucalyptus Oil 7%...........................Anti-inflammatory
Menthol Crystal 11%.........................Topical Analgesic
Wintergreen 0.2%.............................Topical Analgesic
(Methyl Salicylate)

Uses

For the temporary relief of minor aches & pains of muscles and joints associated with:

- arthritis & rheumatism
- backaches
- strains
- bruises
- sprains
- leg cramps

Warnings

For external use only.
When using this product: Discontinue use if excessive irritation of the skin develops. Avoid contact with eyes and mucous membranes. Do not apply to wounds or damaged skin. Do not bandage tightly. Do not use with a heating pad.
Discontinue use of this product and consult a doctor if:

- Condition worsens
- symptoms persist for more than 10 days or clear up and occur again within a few days
- redness is present
- Severe skin irritation occurs
- or in conditions affecting children under 12 years of age, consult a physician immediately.

If pregnant or breast-feeding, ask a health care professional before use

Keep out of reach of children. If swallowed, get medical help or contact a Poison Control immediately

Directions

- Rub well on the affected area. Repeat 3 to 4 times daily.
- For children under 12, consult a doctor before use.

Other information

Store in a cool dry place 20° to 25° C (68° to 77° F). This product may cause allergic reaction in some individuals. Test on small area before use. Do not use if seal is broken.

Inactive Ingredients

Beeswax, Borneol, Cassia Oil, Cinnamon Leaf Oil, Citronella Oil, Clove Oil, Nutmeg Oil, Paraffin Wax, Peppermint Oil, Soft White Paraffin